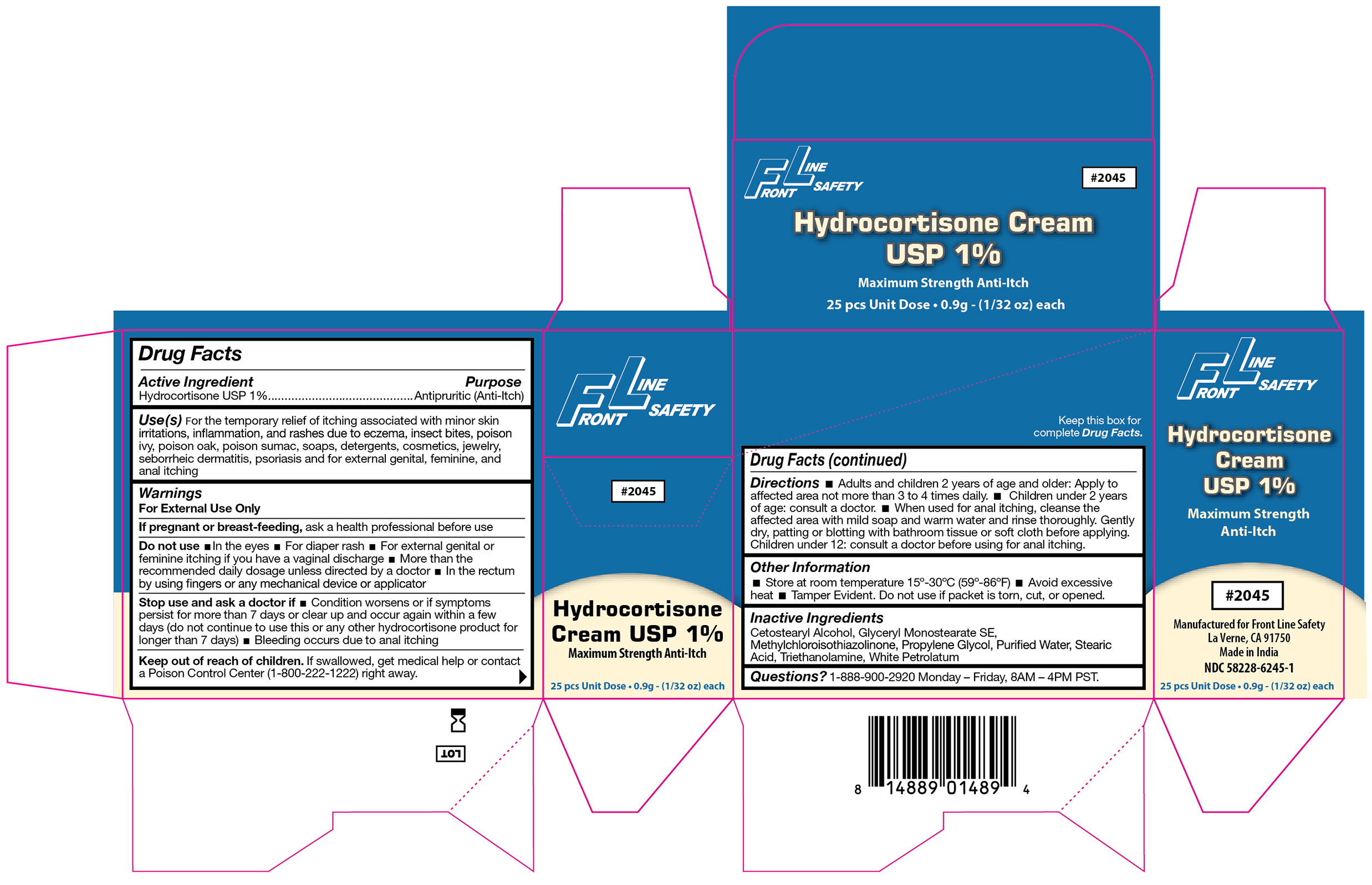 DRUG LABEL: Hydrocortisone Cream 1%
NDC: 58228-6245 | Form: CREAM
Manufacturer: Front Line Safety
Category: otc | Type: HUMAN OTC DRUG LABEL
Date: 20251215

ACTIVE INGREDIENTS: HYDROCORTISONE 1 g/100 g
INACTIVE INGREDIENTS: WATER; GLYCERYL STEARATE SE; PROPYLENE GLYCOL; WHITE PETROLATUM; METHYLCHLOROISOTHIAZOLINONE; STEARIC ACID; CETOSTEARYL ALCOHOL; TROLAMINE

FL-2045

Active Ingredient

Hydrocortisone USP 1%

Purpose

Antipruritic (Anti-Itch)

Use(s)

For the Temporary relief of itching associated with minor skin irritations, inflammation, and rashes due to eczema, insect bites, poison ivy, poison oak, poison sumac, soaps, detergents, cosmetics, jewelry, seborrheic dermatitis, psoriasis, and for external genital, feminine, and anal itching

Warnings

For External Use Only

If pregnant or breastfeeding

Ask a health professional before use

Do not use

• In the eyes • For diaper rash • For external genital or feminine itching if you have a vaginal discharge • More than the recommended daily dosage unless directed by a doctor • In the rectum by using fingers or any mechanical device or applicator

Stop use and ask a doctor if

• Condition worsens or if symptoms persist for more than 7 days or clear up and occur again with a few days (do not continue to use this or any other hydrocortisone product for longer than 7 days)

• Bleeding occurs due to anal itching

Keep out of reach of children

If swallowed, get medical help or contact a Poison Control Center (1-800-222-1222) right away.

Directions

• Adults and Children 2 years of age and older: Apply to affected area not more than 3 to 4 times daily.

• Children under 2 years of age: Consult a doctor

• When used for anal itching, cleanse the affected area with mild soap and warm water and rinse thoroughly. Gently dry, patting or blotting with bathroom tissue or soft cloth before applying.

• Children under 12: Consult a doctor before using for anal itching.

Other Information

• Store at room temperature 15º-30ºC (59º-86ºF) • Avoid excessive heat • Tamper Evident. Do not use if packet is torn, cut or opened.

Inactive Ingredients

Cetostearyl Alcohol, Glyceryl Monostearate SE, Methylchloroisothiazolinone, Propylene Glycol, Purified Water, Stearic Acid, Triethanolamine, White Petrolatum

Questions?

1-888-900-2920 Monday - Friday, 8AM - 4PM PST

Label

FL-2045